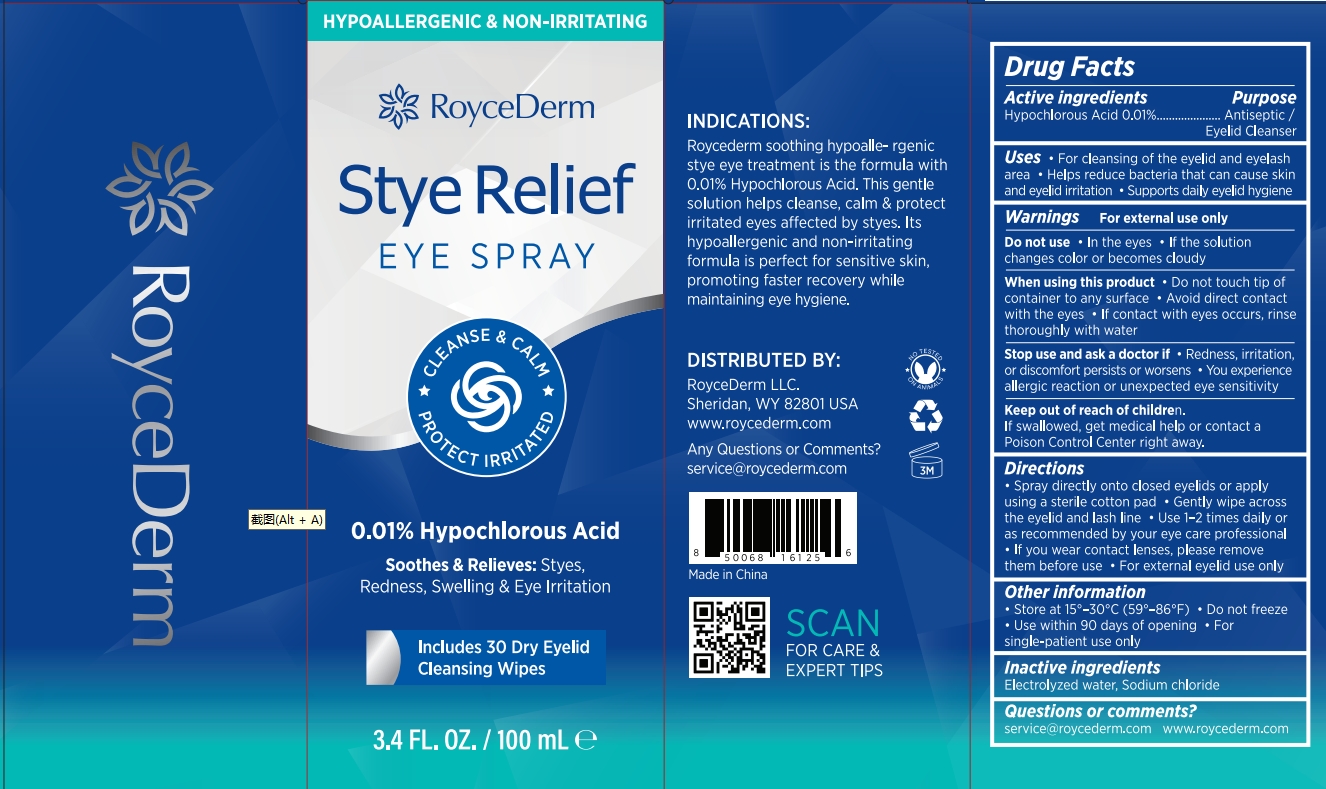 DRUG LABEL: RoyceDerm Stye Relief Eye Spray.
NDC: 85424-006 | Form: SPRAY
Manufacturer: RoyceDerm LLC
Category: otc | Type: HUMAN OTC DRUG LABEL
Date: 20250728

ACTIVE INGREDIENTS: HYPOCHLOROUS ACID 0.01 g/100 g
INACTIVE INGREDIENTS: WATER; SODIUM CHLORIDE

Initial Drug Listing - RoyceDerm Stye Relief Eye Spray

ACTIVE INGREDIENT

Hypochlorous Acid 0.01%

PURPOSE

Antiseptic / Eyelid Cleanser

DOSAGE AND ADMINISTRATION

For cleansing of the eyelid and eyelash
area

Helps reduce bacteria that can cause skin
and eyelid irritation

Supports daily eyelid hygiene

WARNINGS

For external use only

DO NOT USE

In the eyes · If the solution changes color or becomes cloudy

ASK DOCTOR

- Redness, irritation, or discomfort persists or worsens
- You experience allergic reaction or unexpected eye sensitivity

WHEN USING

- Do not touch tip of container to any surface
- Avoid direct contact with the eyes
- If contact with eyes occurs, rinse thoroughly with water

STOP USE

- Redness, irritation,or discomfort persists or worsens
- You experience allergic reaction or unexpected eye sensitivity

KEEP OUT OF REACH OF CHILDREN

If swallowed, get medical help or contact a Poison Control Center right away.

INDICATIONS AND USAGE

- Spray directly onto closed eyelids or applyusing a sterile cotton pad
- Gently wipe acrossthe eyelid and lash line
- Use 1-2 times daily oras recommended by your eye care professional
- If you wear contact lenses, please removethem before use
- For external eyelid use only

OTHER SAFETY INFORMATION

- Store at 15°-30°C(59°-86°F)
- Do not freeze
- Use within 90 days of opening
- Forsingle-patient use only

INACTIVE INGREDIENT

Electrolyzed water, Sodium chloride

QUESTIONS

- service@roycederm.com
- www.roycederm.com